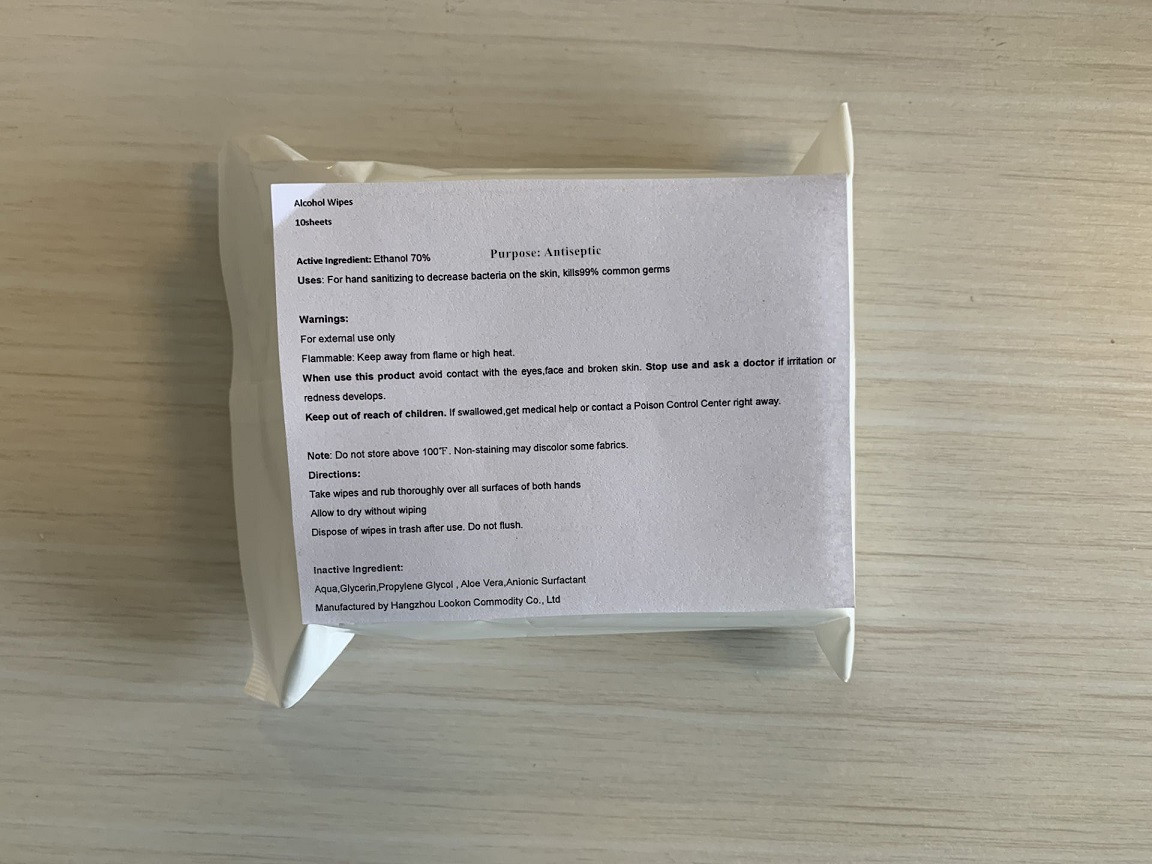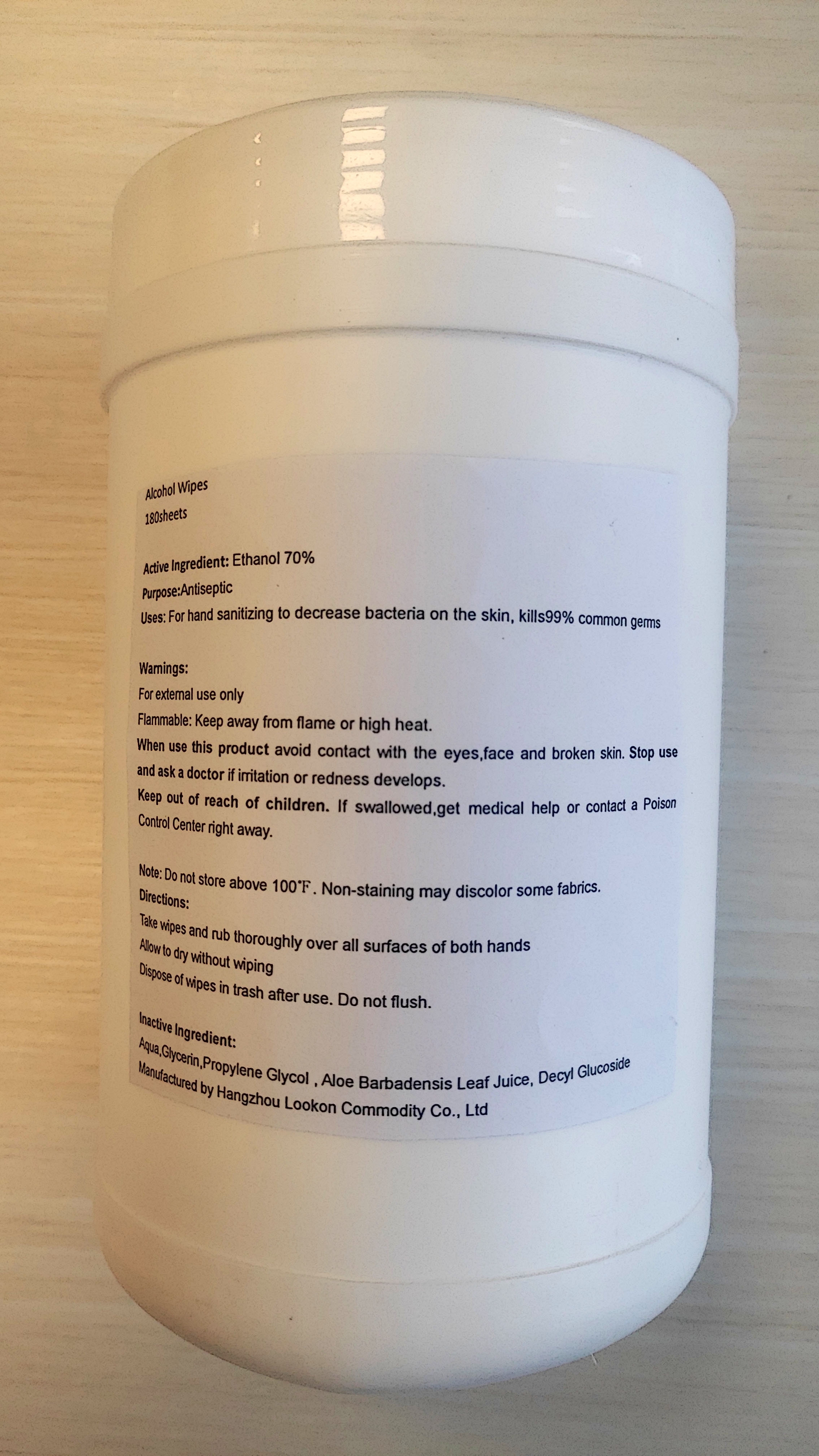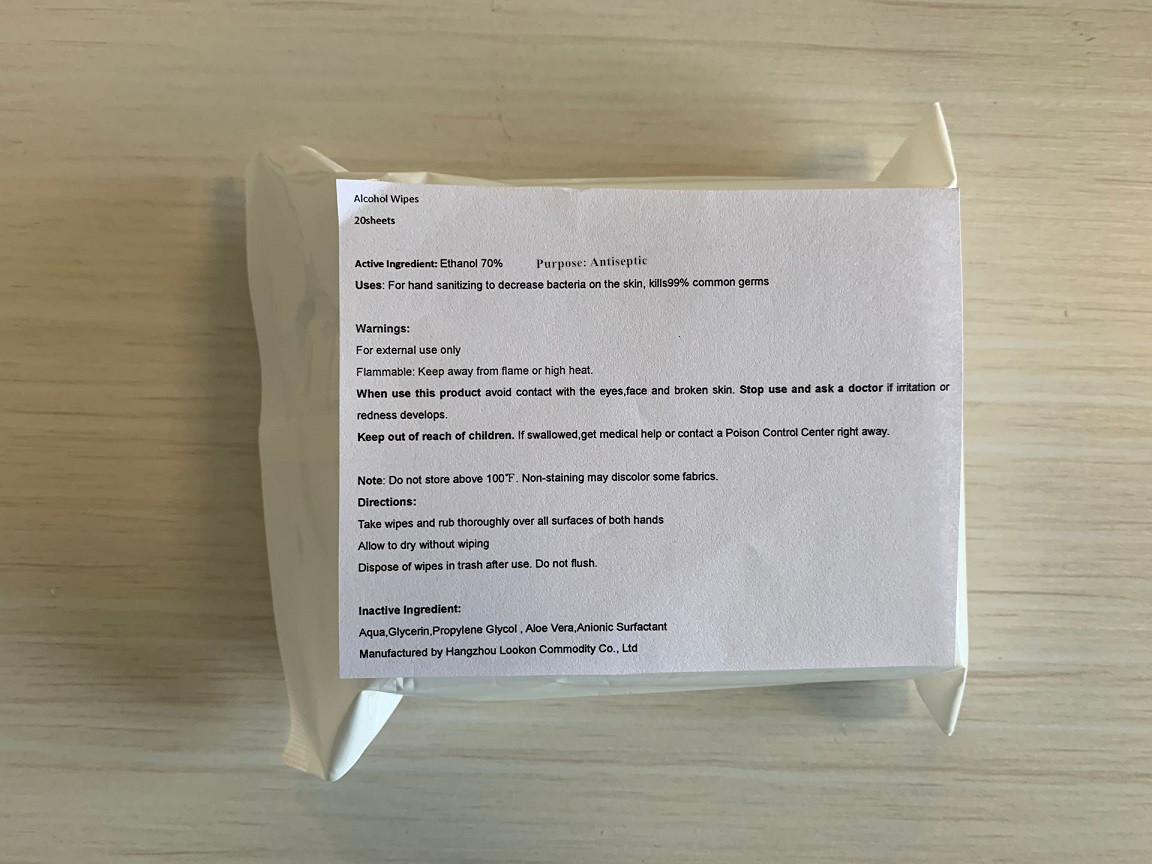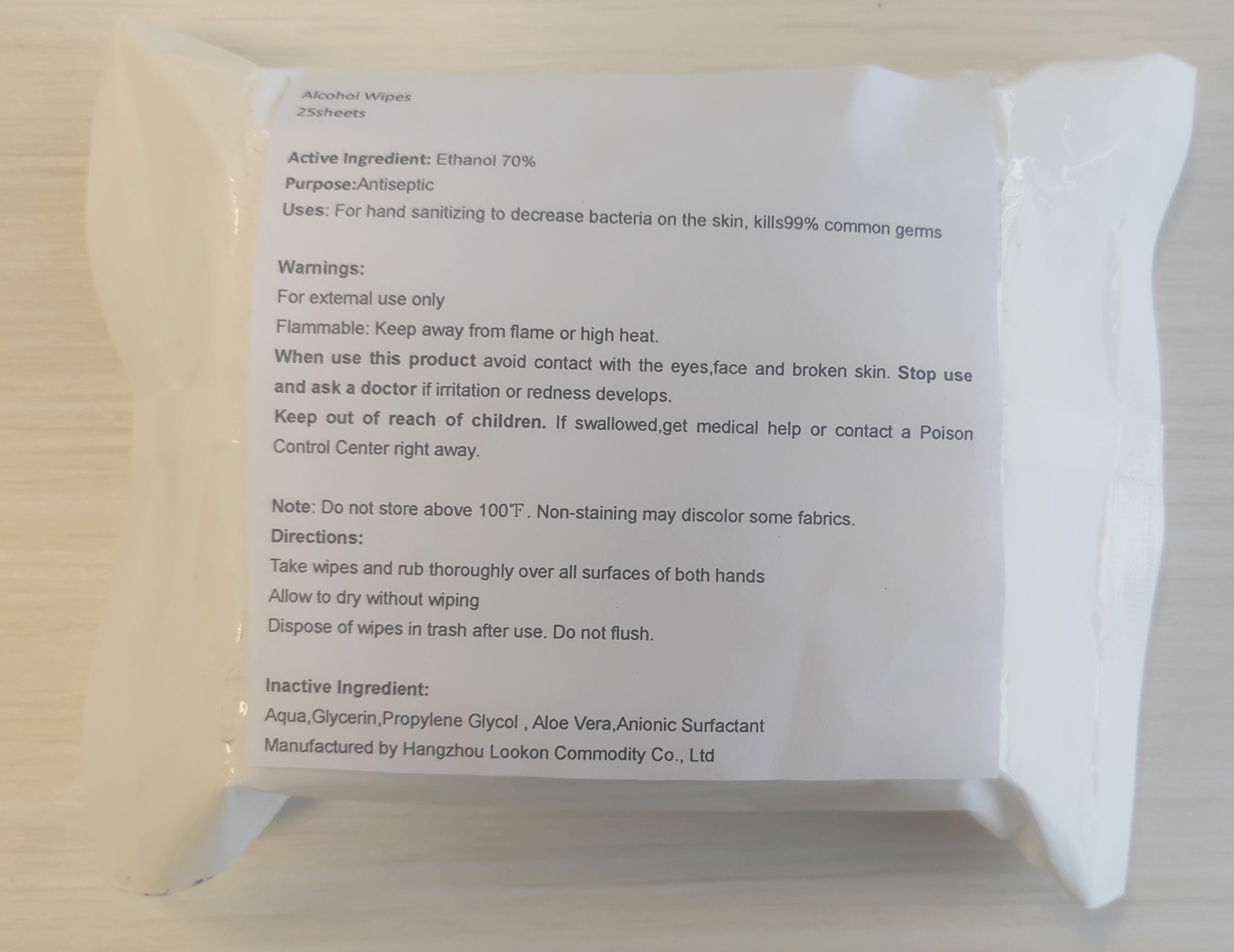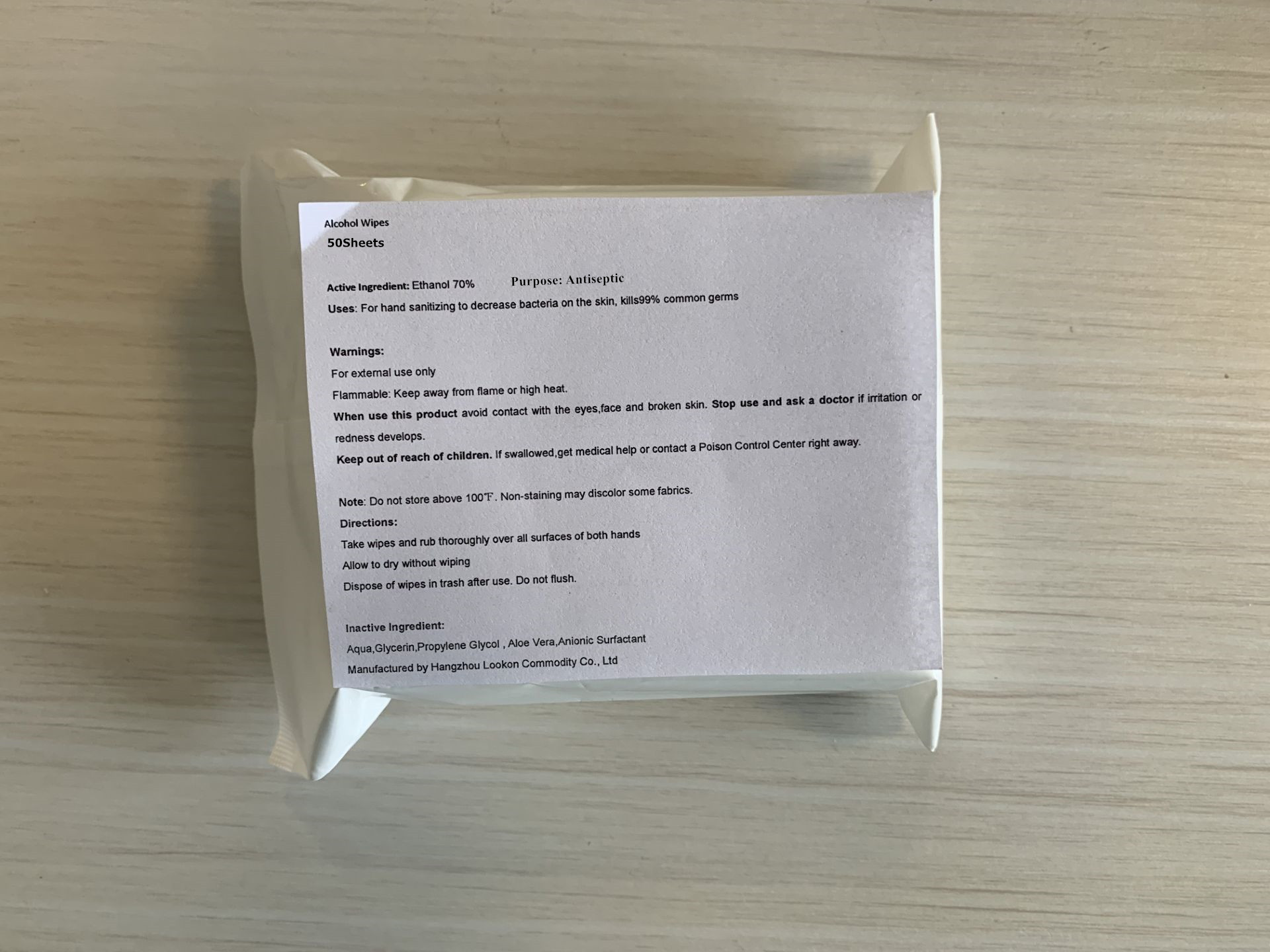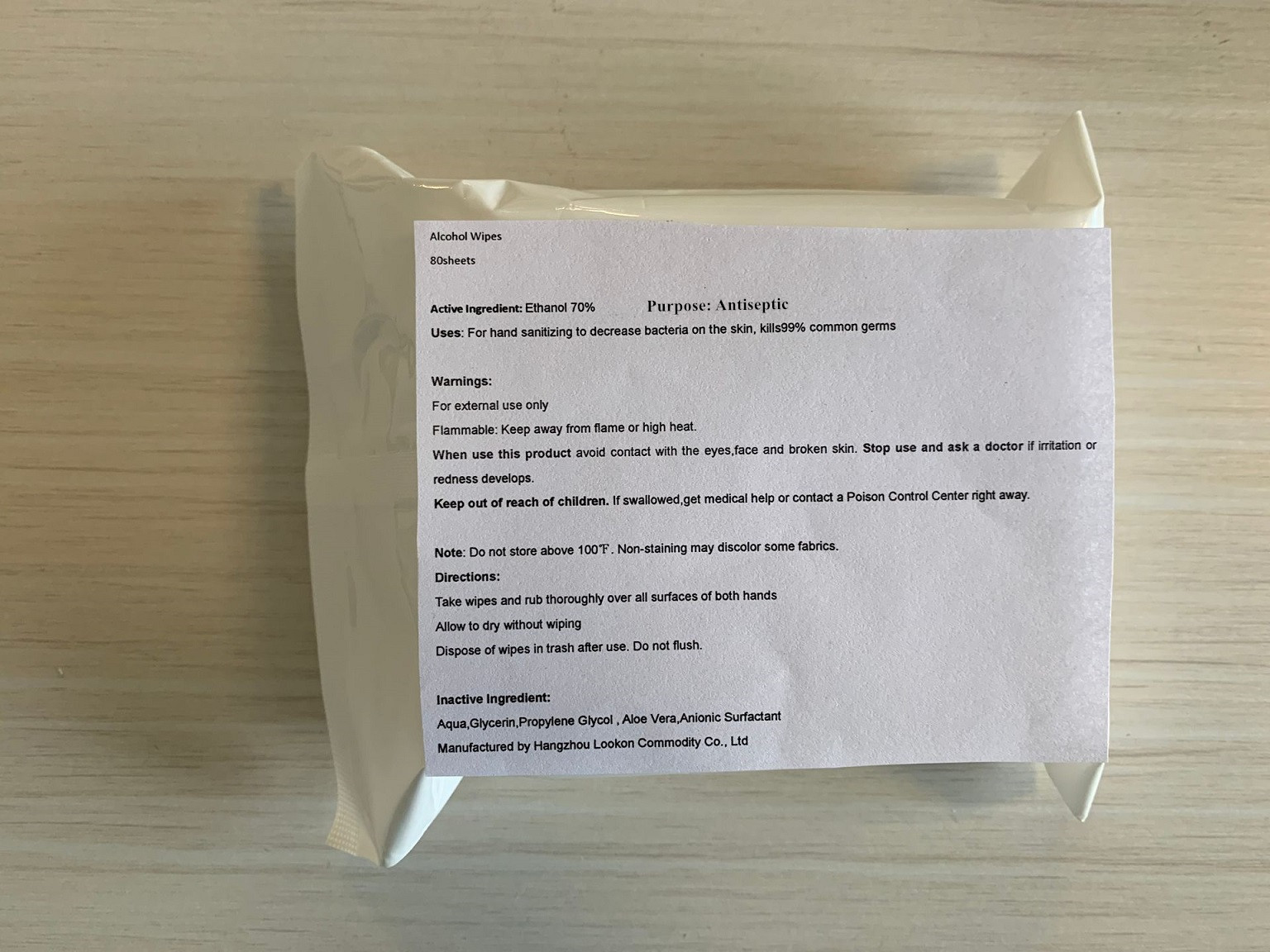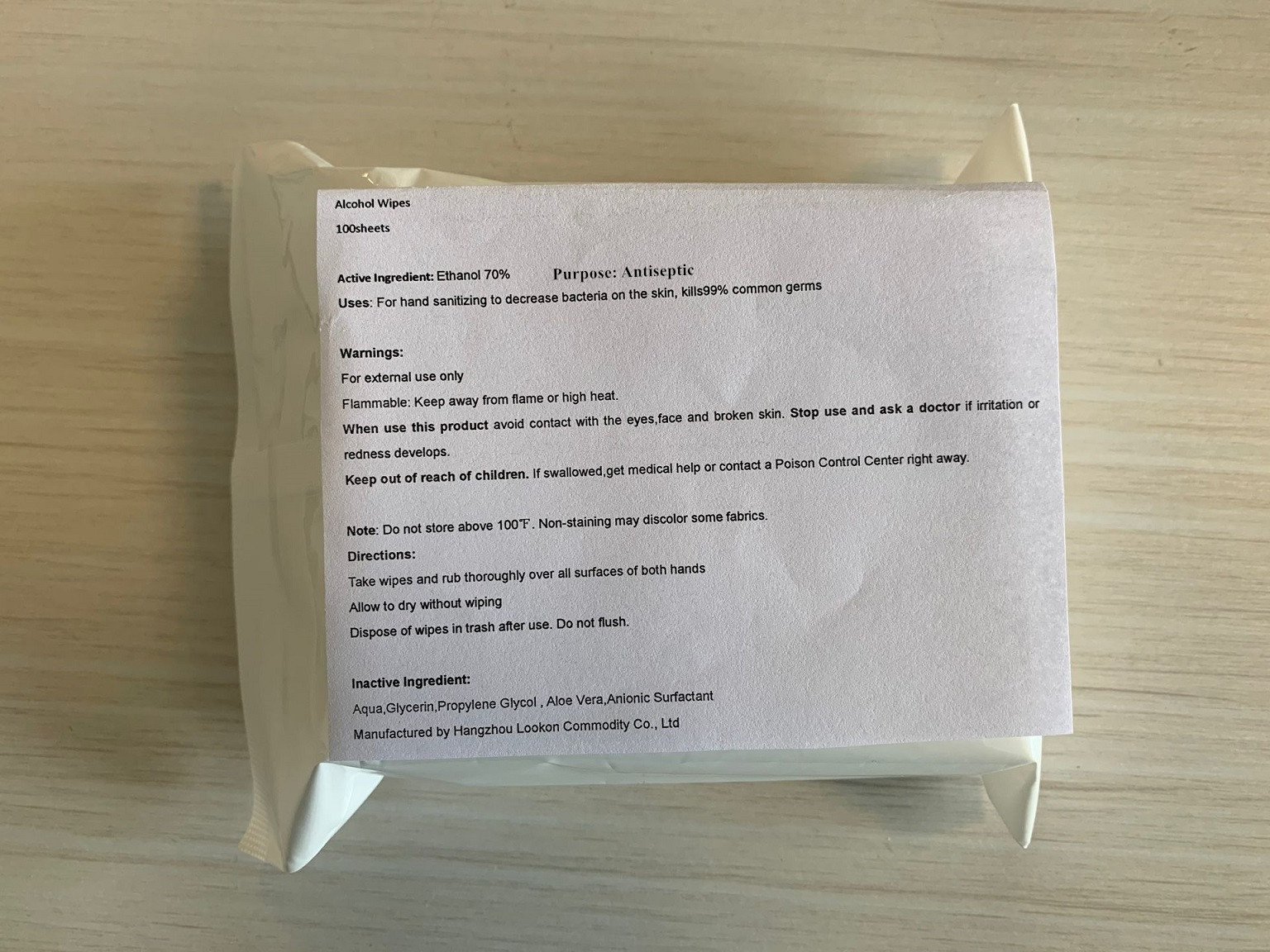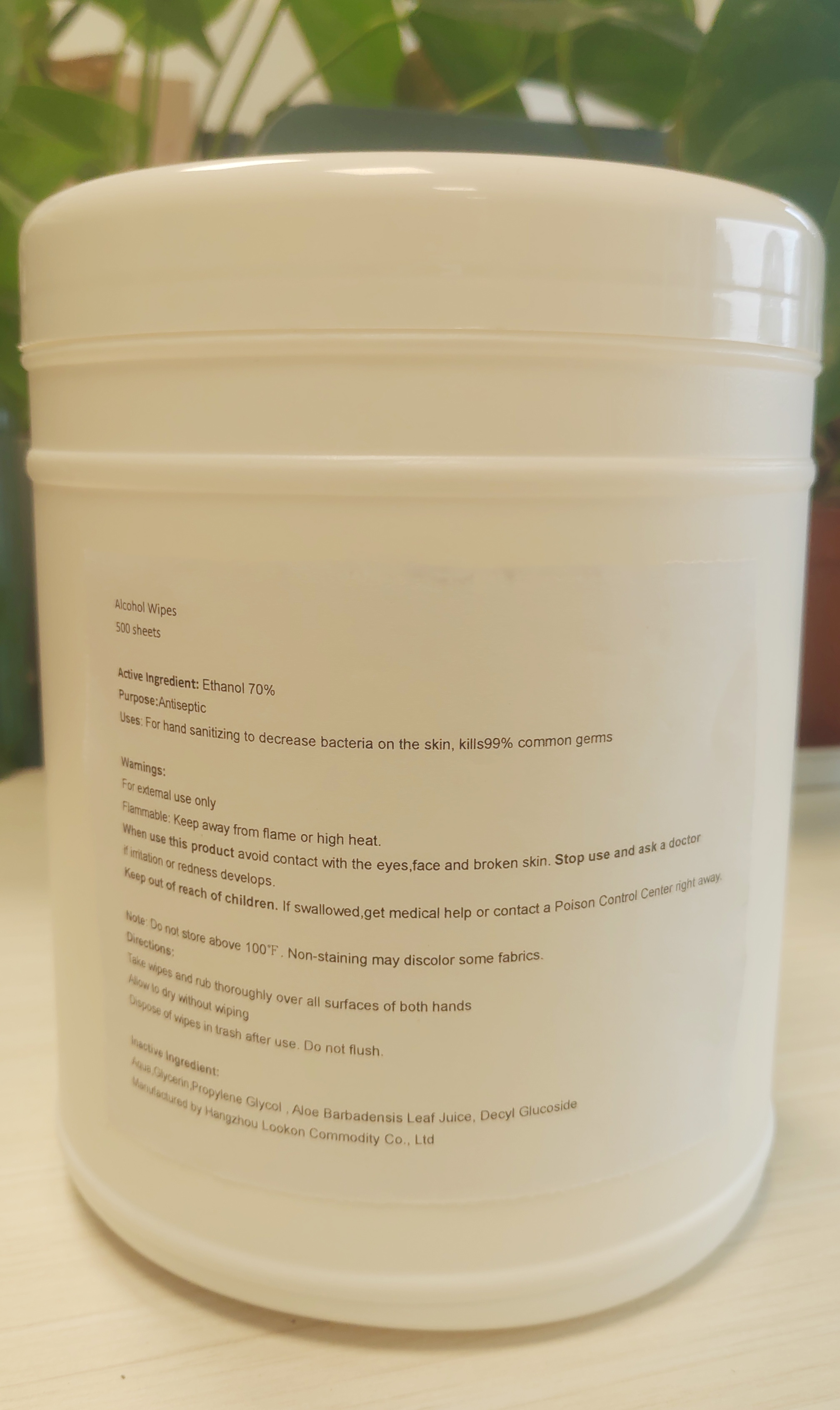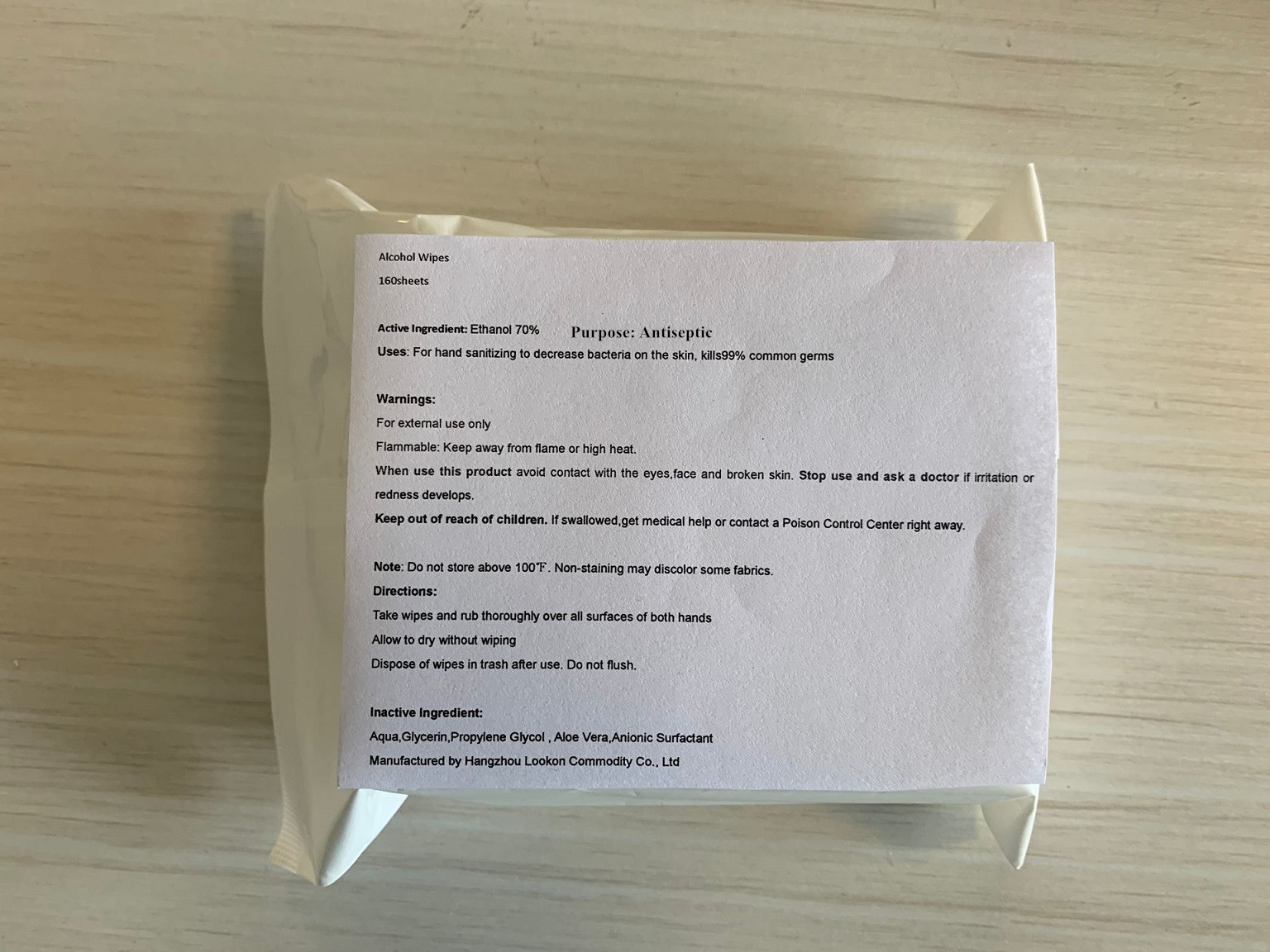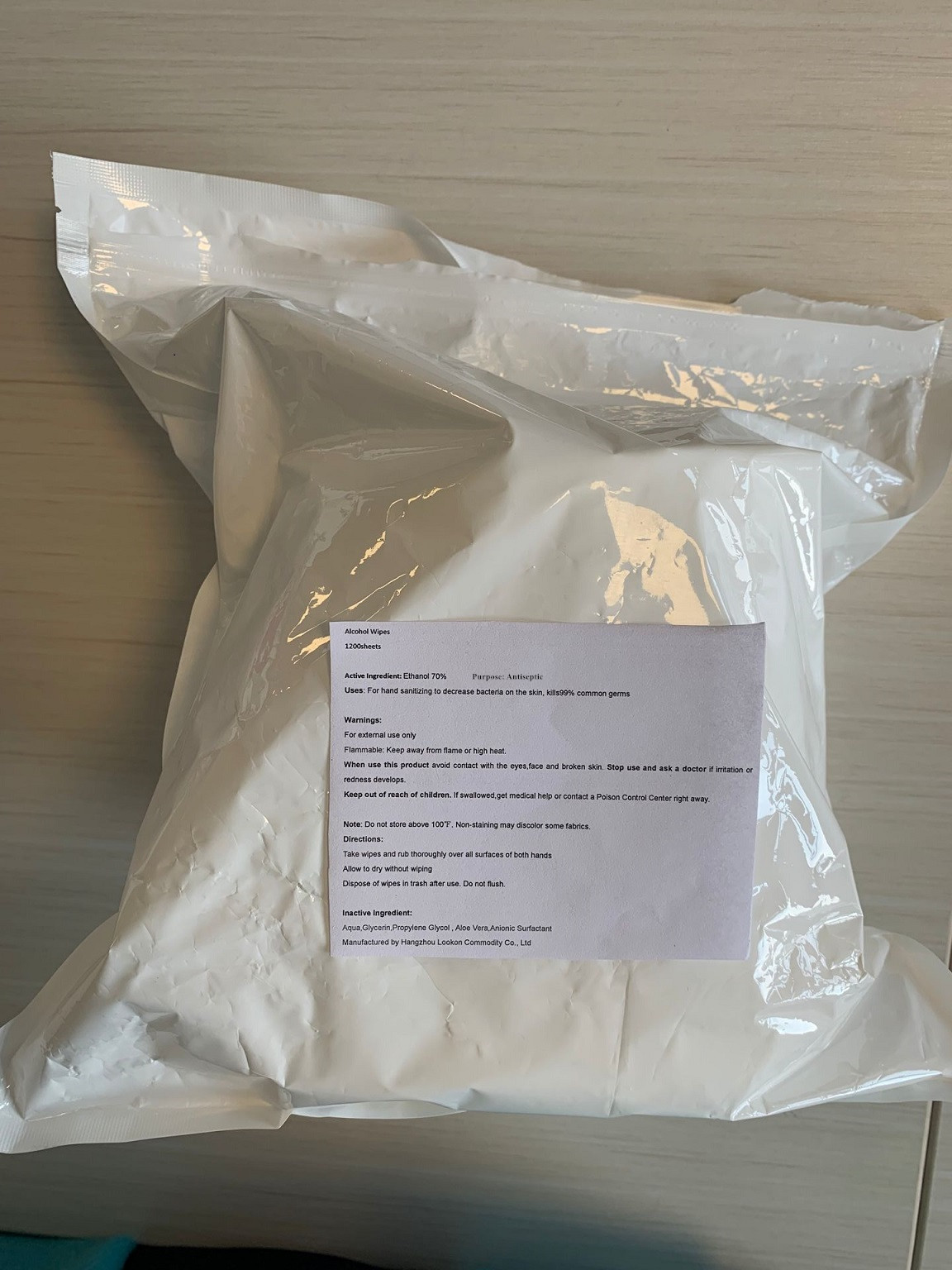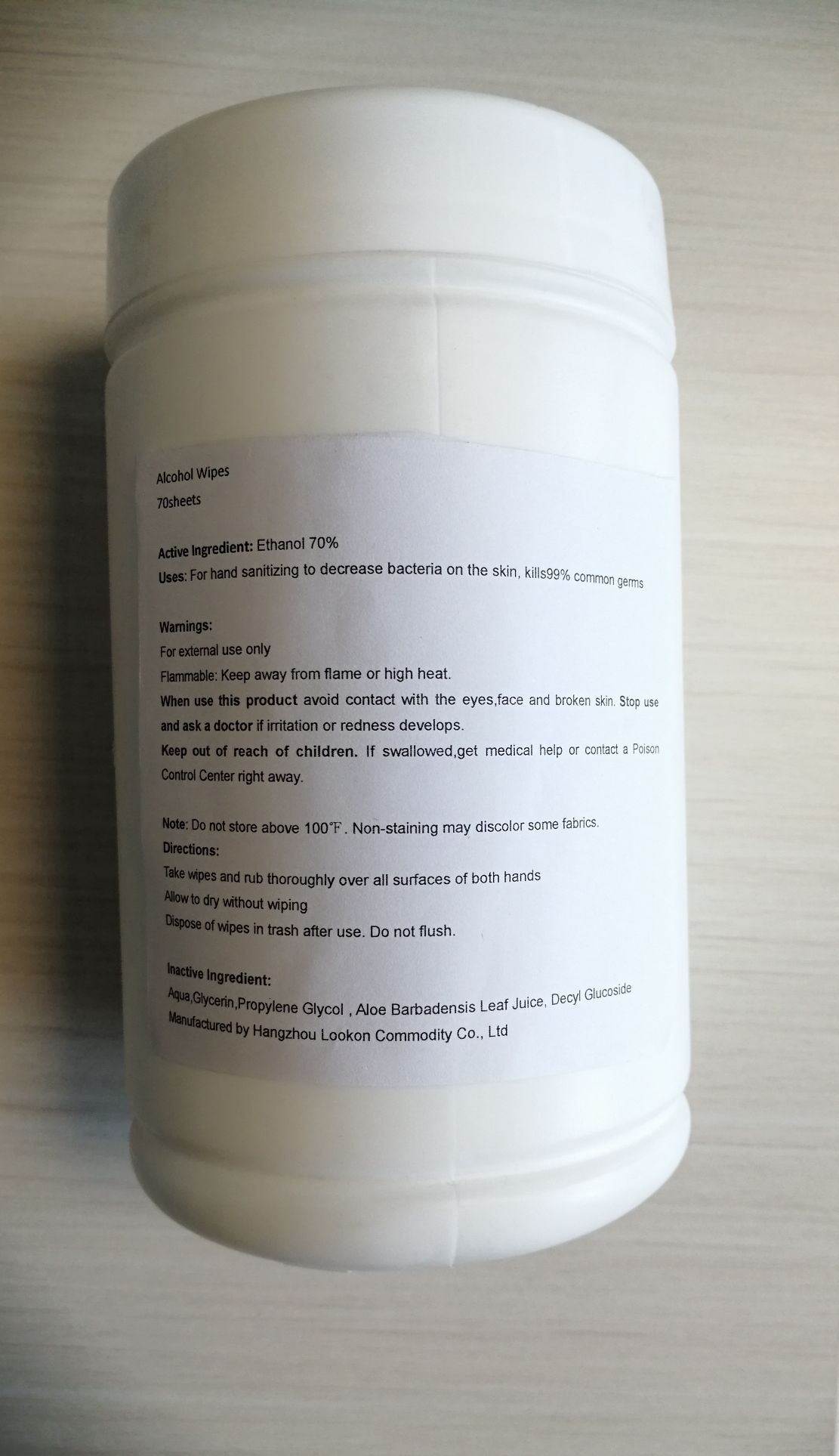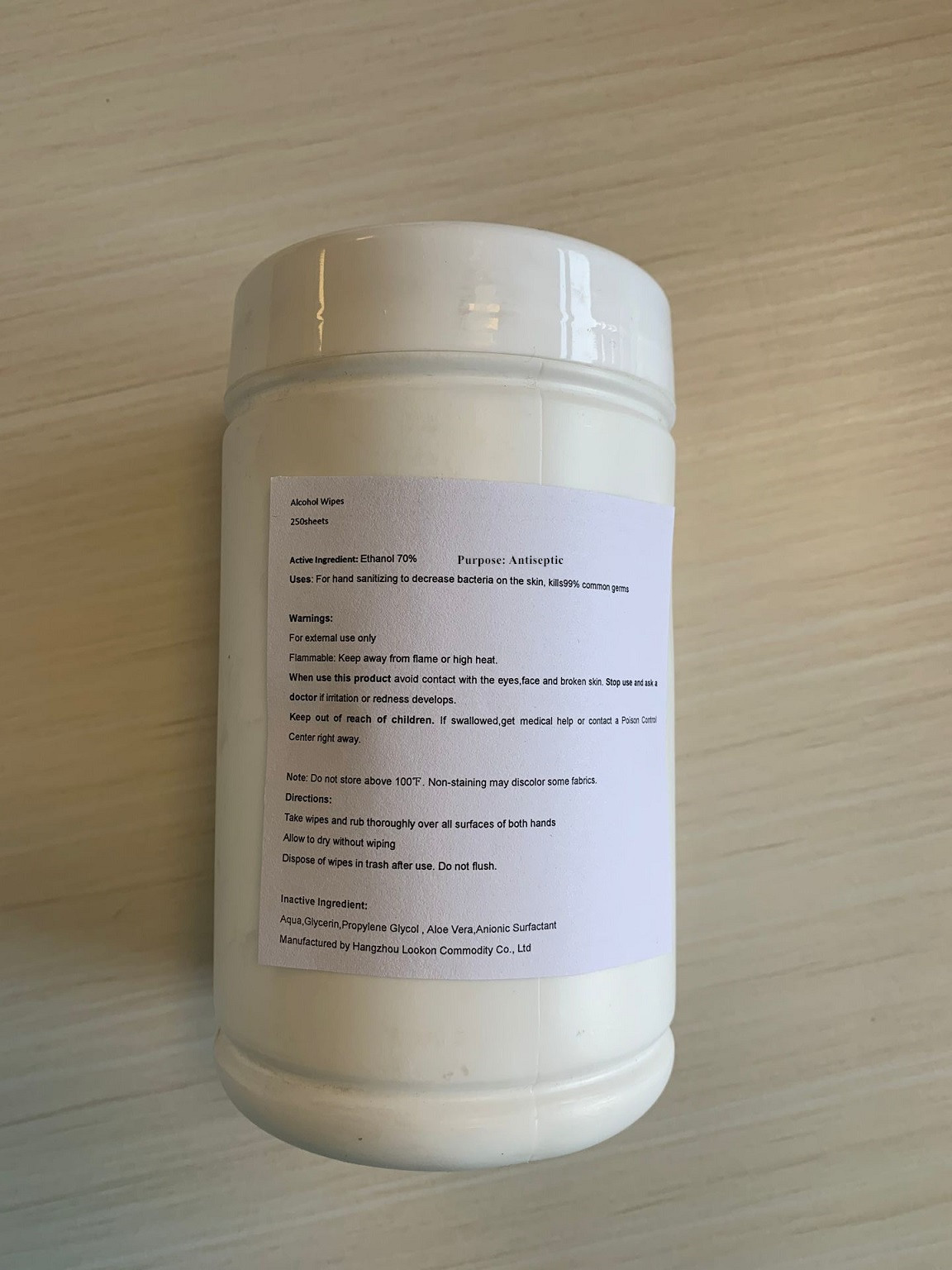 DRUG LABEL: Alcohol Wipes
NDC: 74835-005 | Form: CLOTH
Manufacturer: Hangzhou Lookon Commodity Co., Ltd
Category: otc | Type: HUMAN OTC DRUG LABEL
Date: 20201213

ACTIVE INGREDIENTS: ALCOHOL 0.7 1/1 1
INACTIVE INGREDIENTS: ALOE VERA LEAF; GLYCERIN; WATER; PROPYLENE GLYCOL; DECYL GLUCOSIDE

Alcohol Wipes

Active Ingredient

Ethanol 70%

Purpose

Antiseptic

Uses

For hand sanitizing to decrease bacteria on the skin, kills99% common germs

Warnings

For external use only

Flammable: Keep away from flame or high heat.

When use this product avoid contact with the eyes,face and broken skin.

Stop use

Stop use and ask a doctor if irritation or redness develops.

Keep out of reach of children. If swallowed,get medical help or contact a Poison Control Center right away.

Note

Do not store above 100℉. Non-staining may discolor some fabrics.

Inactive Ingredient

Aqua,Glycerin,Propylene Glycol , Aloe Vera,Anionic Surfactant

Or

Aqua,Glycerin,Propylene Glycol , Aloe Barbadensis Leaf Juice, Decyl Glucoside

Directions

Take wipes and rub thoroughly over all surfaces of both hands

Allow to dry without wiping

Dispose of wipes in trash after use. Do not flush.

Package Label

Alcohol Wipes

10sheets

NDC: 74835-005-01

Alcohol Wipes

20sheets

NDC: 74835-005-02

Alcohol Wipes

50sheets

NDC: 74835-005-03

Alcohol Wipes

80sheets

NDC: 74835-005-04

Alcohol Wipes

100sheets

NDC: 74835-005-05

Alcohol Wipes

160sheets

NDC: 74835-005-06

Alcohol Wipes

1200sheets

NDC: 74835-005-07

Alcohol Wipes

250sheets

NDC: 74835-005-08

Package Label

Alcohol Wipes

70sheets

NDC: 74835-005-09

PDP

Alcohol Wipes

25sheets

NDC: 74835-005-10

PDP

Alcohol Wipes

180sheets

NDC: 74835-001-11

PDP

Alcohol Wipes

500sheets

NDC: 74835-005-12